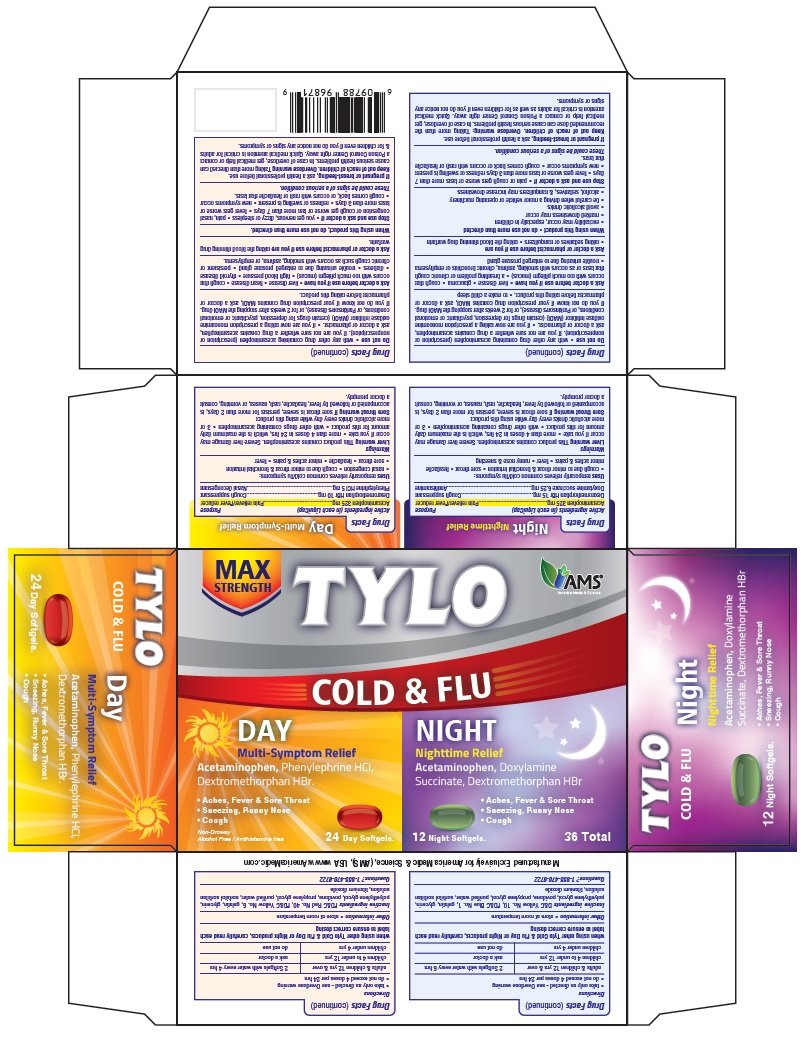 DRUG LABEL: Tylo Cold and Flu
NDC: 49638-113 | Form: CAPSULE, LIQUID FILLED
Manufacturer: America Medic & Science, LLC
Category: otc | Type: HUMAN OTC DRUG LABEL
Date: 20190122

ACTIVE INGREDIENTS: ACETAMINOPHEN 325 mg/1 1; DEXTROMETHORPHAN HYDROBROMIDE 10 mg/1 1; PHENYLEPHRINE HYDROCHLORIDE 5 mg/1 1
INACTIVE INGREDIENTS: FD&C RED NO. 40; FD&C YELLOW NO. 6; GELATIN; GLYCERIN; POLYETHYLENE GLYCOL, UNSPECIFIED; POVIDONE; PROPYLENE GLYCOL; WATER; SORBITOL; TITANIUM DIOXIDE

TYLO COLD & FLU (Day)

Active ingredients (in each LiquiCap)

Acetaminophen 325 mg
Dextromethorphan HBr 10 mg
Phenylephrine HCl 5 mg

Purpose

Pain reliever/fever reducer
Cough suppressant
Nasal decongestant

Uses

- temporarily relieves common cold/flu symptoms:
  - nasal congestion
  - cough due to minor throat and bronchial irritation
  - sore throat
  - headache
  - minor aches & pains
  - fever

Warnings

Liver warning: This product contains acetaminophen. Severe liver damage may occur if you take

- more than 4 doses in 24 hrs, which is the maximum daily amount for this product
- with other drugs containing acetaminophen
- 3 or more alcoholic drinks every day while using this product

Sore throat warning If sore throat is severe, persists for more than 2 days, is accompanied or followed by fever, headache, rash, nausea, or vomiting, consult a doctor promptly.

Do not use

- with any other drug containing acetaminophen (prescription or nonprescription). If you are not sure whether a drug contains acetaminophen, ask a doctor or pharmacist.
- if you are now taking a prescription monoamine oxidase inhibitor (MAOI) (certain drugs for depression, psychiatric or emotional conditions, or Parkinson's disease), or for 2 weeks after stopping the MAOI drug. If you do not know if your prescription drug contains MAOI, ask a doctor or pharmacist before taking this product.

Ask a doctor before use if you have

- liver disease
- heart disease
- cough that occurs with too much phlegm (mucus)
- high blood pressure
- thyroid disease
- diabetes
- trouble urinating due to enlarged prostate gland
- persistent or chronic cough such as occurs with smoking, asthma, or emphysema.

Ask a doctor or pharmacist before use if you are

taking the blood thinning drug warfarin.

When using this product

do not use more than directed.

Stop use and ask a doctor if

- you get nervous, dizzy or sleepless
- pain, nasal congestion or cough get worse or last more than 7 days
- fever gets worse or lasts more than 3 days
- redness or swelling is present
- new symptoms occur
- cough comes back, or occurs with rash or headache that lasts.

These could be signs of a serious condition.

If pregnant or breast-feeding,

ask a health professional before use.

Other Information

Keep out of reach of children.

Overdose warning Taking more than directed can cause serious health problems. In case of overdose, get medical help or contact a Poison Control Center right away. Quick medical attention is critical for adults & for children even if you do not notice any signs or symptoms.

Directions

- take only as directed - see Overdose warning
- do not exceed 4 doses per 24 hrs
- adults & children 12 yrs & over: 2 Softgels with water every 4 hrs
- children 4 to under 12 yrs: ask a doctor
- children under 4 yrs: do not use

DOSAGE AND ADMINISTRATION

when using other Tylo Cold & Flu Day or Night products, carefully read each label to ensure correct dosing

Other information:

store at room temperature

Inactive ingredients

FD&C Red No. 40, FD&C Yellow No. 6, gelatin, glycerin, polyethylene glycol, povidone, propylene glycol, purified water, sorbitol sorbitan solution, titanium dioxide

Questions?

1-855-470-6722

PACKAGE LABEL

TYLO COLD & FLU (Day)

Acetaminophen 325 mg
Dextromethorphan HBr 10 mg
Phenylephrine HCl 5 mg